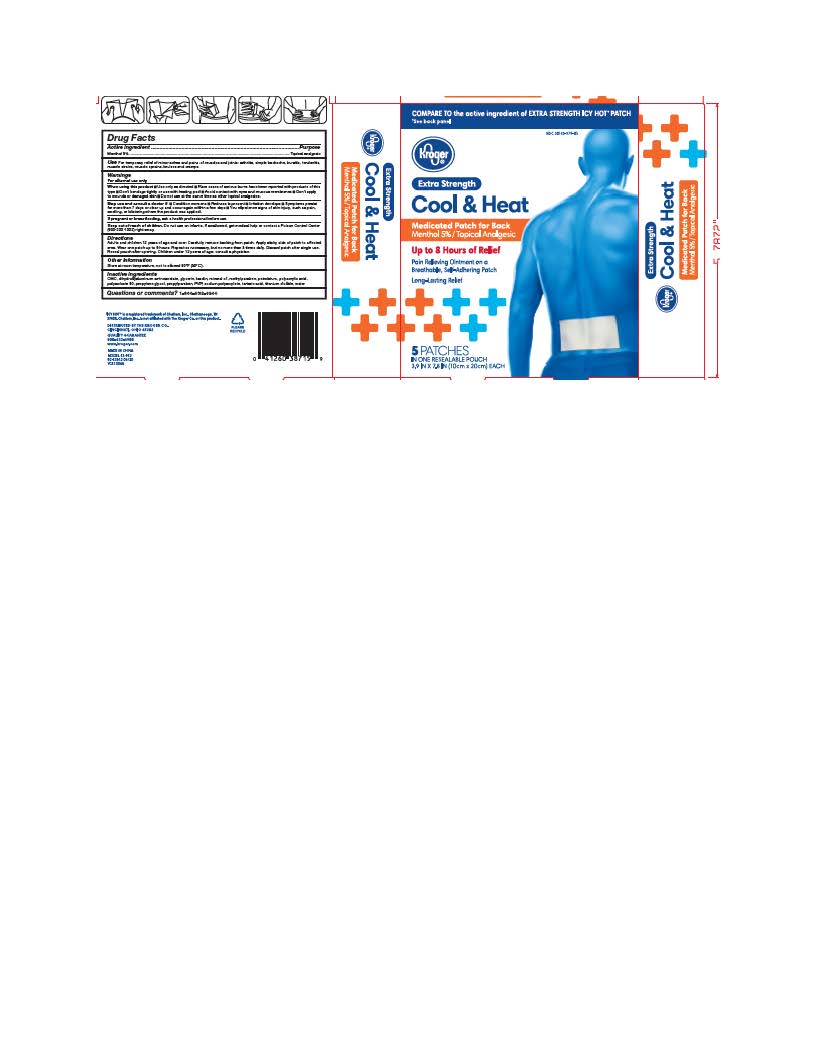 DRUG LABEL: Kroger Hot and Cold Medicated Patch
NDC: 30142-979 | Form: PATCH
Manufacturer: Kroger Company
Category: otc | Type: HUMAN OTC DRUG LABEL
Date: 20251230

ACTIVE INGREDIENTS: MENTHOL 5 g/100 g
INACTIVE INGREDIENTS: MINERAL OIL; CARBOXYMETHYLCELLULOSE; DIHYDROXYALUMINUM AMINOACETATE; GLYCERIN; KAOLIN; METHYLPARABEN; SODIUM POLYACRYLATE (2500000 MW); POLYACRYLIC ACID (250000 MW); POLYSORBATE 80; PROPYLENE GLYCOL; PROPYLPARABEN; POVIDONE, UNSPECIFIED; TARTARIC ACID; TITANIUM DIOXIDE; WATER; PETROLATUM

Kroger Hot and Cold Medicated Patch

ACTIVE INGREDIENT

Active Ingredient ...............................................................................................Purpose
Menthol 5%...............................................................................................Topical Analgesic

INACTIVE INGREDIENT

CMC, Dihydroxy aluminum Aminoacetate, Glycerin, Kaolin, Mineral Oil, Methylparaben, Petrolatum, Polyacrylic Acid, Polysorbate 80, Propylene Glycol, Propylparaben, PVP, Sodium Polyacrylate, Tartaric Acid, Titanium Dioxide, Water

KEEP OUT OF REACH OF CHILDREN

Do not use on infants. If swallowed, get medical help or contact a Poison Control Center right away.

INDICATIONS & USAGE

Temporarily relieves minor aches and pains of muscles and joins associated with: ■ arthritis ■ simple backache ■ bursitis ■ tendonitis
■ strains ■ sprains ■ bruises ■ cramps

WARNINGS

For External Use Only.

DOSAGE & ADMINISTRATION

Adults and children 12 years of age and over: Carefully remove backing from patch. Apply sticky side of patch to affected area.

Wear one patch up to 8 hours. Repeat as necessary, but no more than 4 times daily. Reseal pouch after opening.

Children under 12 years of age: Consult a physician.

PURPOSE

Topical Analgesic

When using this product

Use only as directed ■ Don’t bandage tightly or use with heating pad
■ Avoid contact with eyes and mucous membranes ■ Don’t apply to wounds or damaged skin.

Stop use and ask a doctor

If condition worsens ■ If redness is present ■ If irritation develops
■ If symptoms persist for more than 7 days or clear up and occur again within a few days.

If pregnant or breastfeeding

ask a health professional before use.